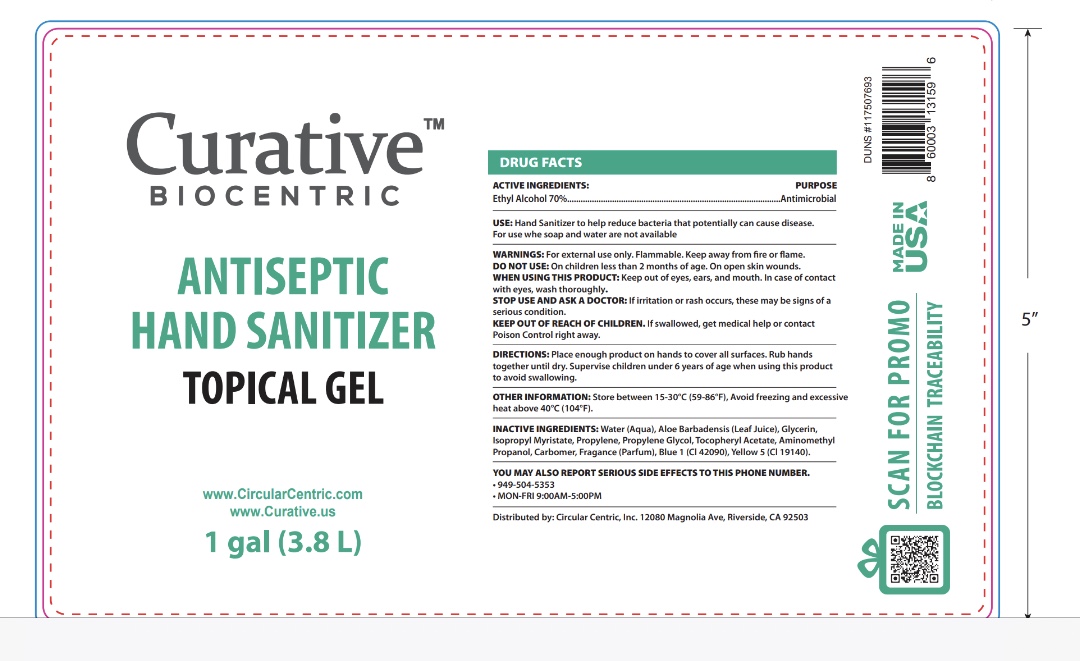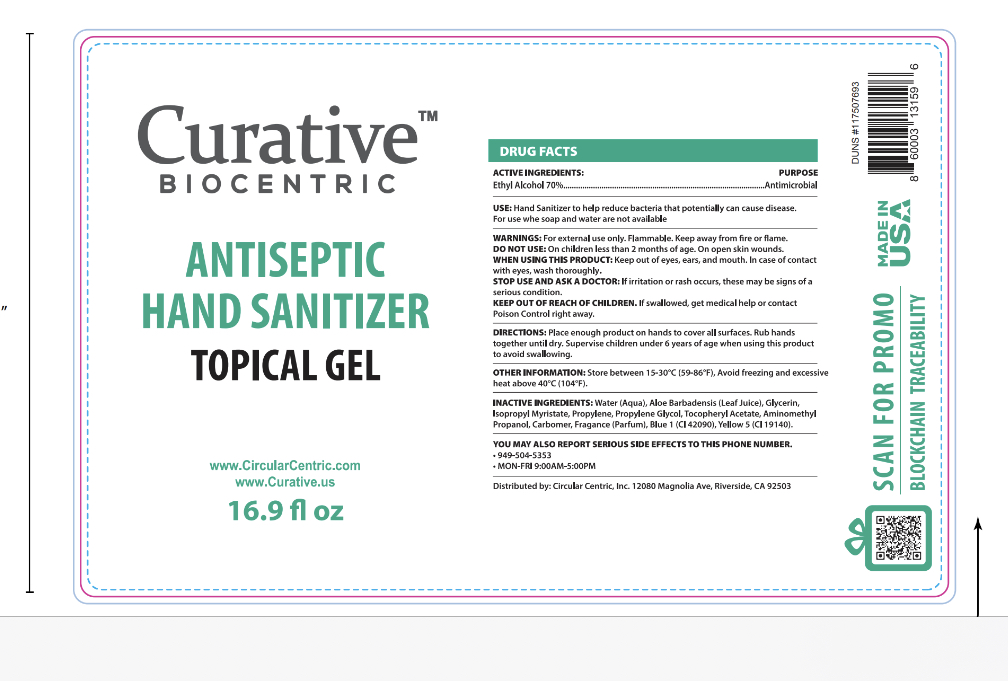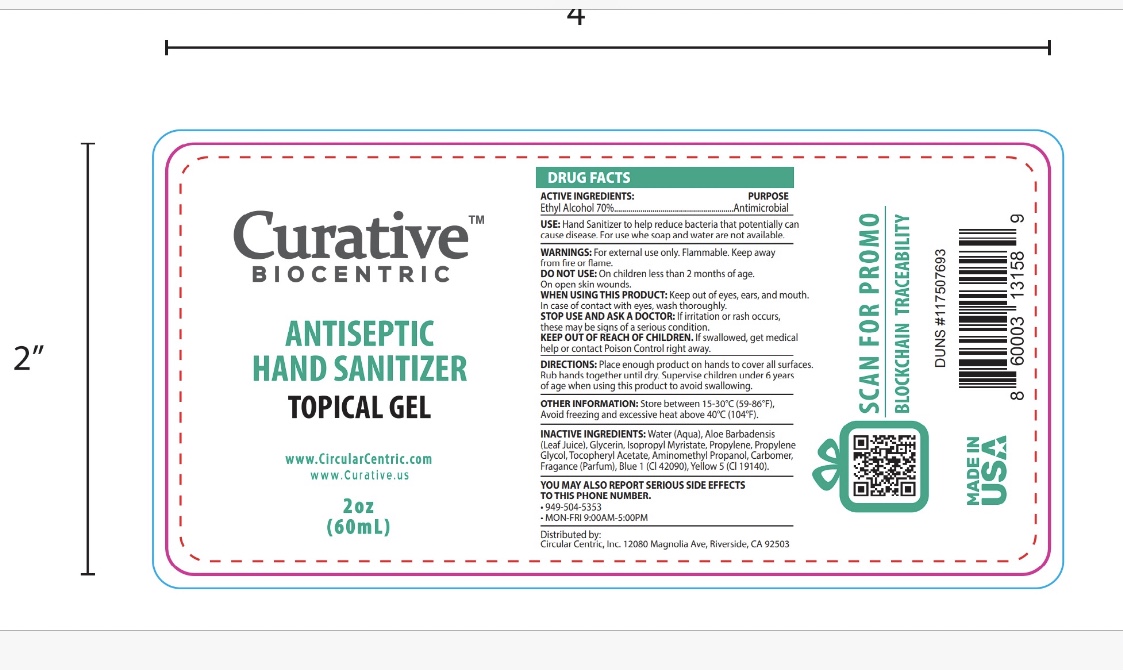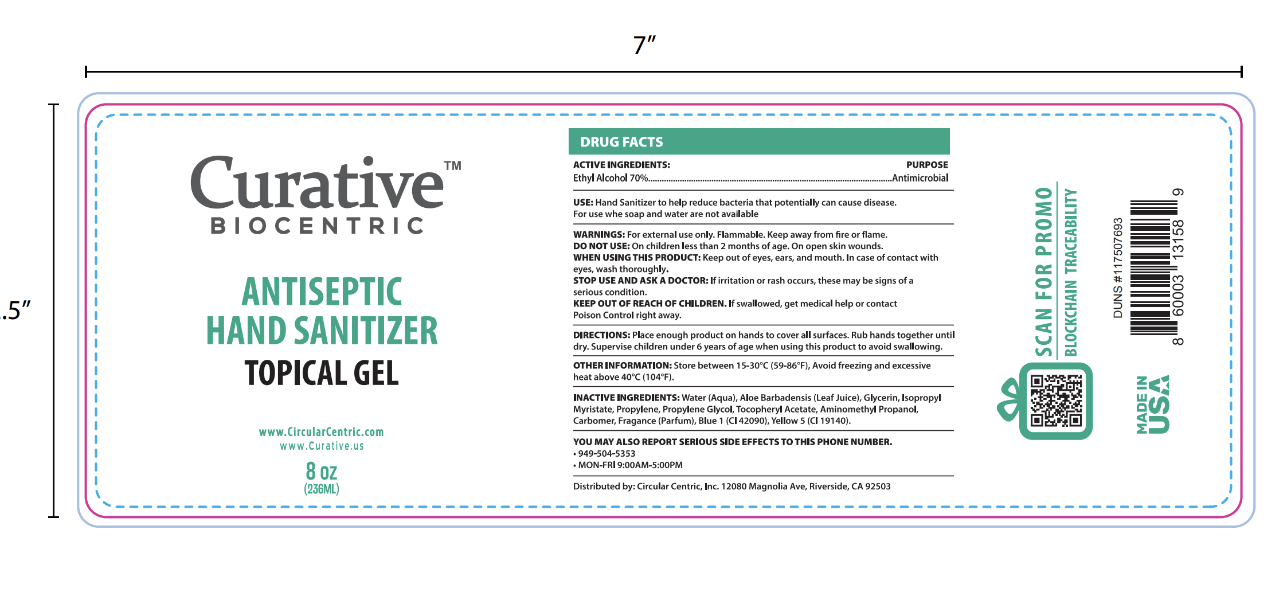 DRUG LABEL: Curative Biocentric Antiseptic Hand Sanitizer
NDC: 77094-888 | Form: GEL
Manufacturer: Circular Centric, Inc.
Category: otc | Type: HUMAN OTC DRUG LABEL
Date: 20200724

ACTIVE INGREDIENTS: ALCOHOL 70 mL/100 mL
INACTIVE INGREDIENTS: ISOPROPYL MYRISTATE 0.5 mL/100 mL; PROPYLENE GLYCOL 0.5 mL/100 mL; .ALPHA.-TOCOPHEROL 0.005 mL/100 mL; AMINOMETHYLPROPANOL 0.1 mL/100 mL; ALOE VERA LEAF 0.005 mL/100 mL; FD&C BLUE NO. 1 0.00001 mL/100 mL; GLYCERIN 2 mL/100 mL; CARBOMER 940 0.3 mL/100 mL; WATER; FD&C YELLOW NO. 5 0.00001 mL/100 mL

Curative Biocentric Antiseptic Hand Sanitizer

This is a hand sanitizer manufactured according to the Temporary Policy for Preparation of Certain Alcohol-Based Hand Sanitizer Products During the Public Health Emergency (CoViD-19); Guidance for Industry.

The hand sanitizer is manufactured using only the following United States Pharmacopoeia (USP) grade ingredients in the preparation of the product (percentage in final product formulation):

Alcohol (ethanol) (USP or Food Chemical Codex (FCC) grade) (80%, volume/volume (v/v)) in an aqueous solution denatured according to Alcohol and Tobacco Tax and Trade Bureau regulations in 27 CFR part 20.

1. Glycerol (2.00% v/v).
2. Carbomer Homopolymer Type C (0.30% v/v).
3. Sterile distilled water or boiled cold water
4. Fragrance Cucumber (0.004% v/v)
5. FD&C Blue No. 1 and FD&C Yellow No. 5
6. Propylene Glycol (0.50% v/v)
7. Aminonethyl propanol (0.10% v/v)
8. Vitamin E (0.005% v/v)
9. Aloe Vera Leaf (0.005% v/v)
10. Isopropyl Myristate (0.50% v/v)

The firm does not add other active or inactive ingredients than stated above. Different or additional ingredients may impact the quality and potency of the product.

Active Ingredient(s)

Alcohol 70% v/v. Purpose: Antiseptic

Purpose

Antiseptic, Hand Sanitizer

Use

Hand Sanitizer to help reduce bacteria that potentially can cause disease. For use when soap and water are not available.

Warnings

For external use only. Flammable. Keep away from fire or flame

Do not use

- in children less than 2 months of age
- on open skin wounds

When using this product keep out of eyes, ears, and mouth. In case of contact with eyes, rinse eyes thoroughly with water.
Stop use and ask a doctor if irritation or rash occurs. These may be signs of a serious condition.
Keep out of reach of children. If swallowed, get medical help or contact a Poison Control Center right away.

Stop use and ask a doctor if irritation or rash occurs. These may be signs of a serious condition.

Keep out of reach of children. If swallowed, get medical help or contact a Poison Control Center right away.

Directions

- Place enough product on hands to cover all surfaces. Rub hands together until dry.
- Supervise children under 6 years of age when using this product to avoid swallowing.

Other information

- Store between 15-30C (59-86F)
- Avoid freezing and excessive heat above 40C (104F)

Inactive ingredients

glycerin, carbomer, fragrance (parfum),, propylene glycol, aminomethyl propanol, vitamine e, aloe vera leaf, blue no. 1, yellow no. 5 purified water (aqua) USP

Package Label - Principal Display Panel

60mL NDC 77094-888-02

236mL NDC 77094-888-08

500mL NDC 77094-888-16

3785mL NDC 77094-888-01